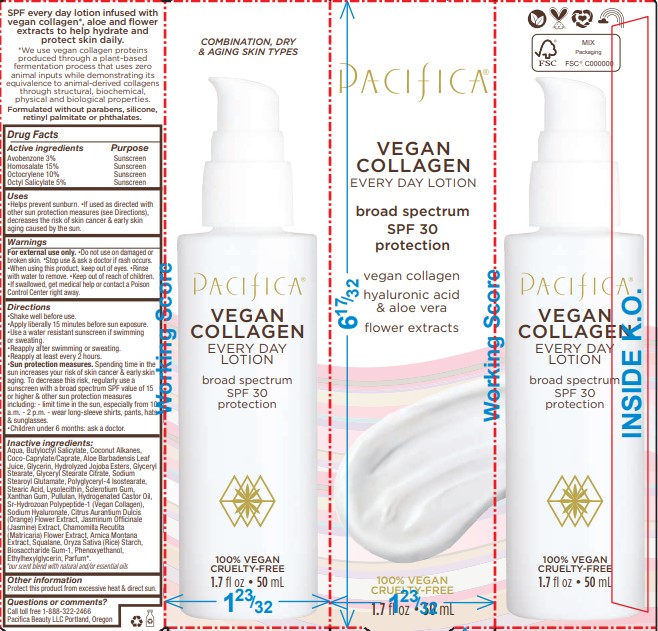 DRUG LABEL: Vegan Collagen Every Day SPF 30
NDC: 61197-510 | Form: LOTION
Manufacturer: Pacifica Beauty, LLC
Category: otc | Type: HUMAN OTC DRUG LABEL
Date: 20250103

ACTIVE INGREDIENTS: OCTOCRYLENE 10 g/100 mL; OCTISALATE 5 g/100 mL; AVOBENZONE 3 g/100 mL; HOMOSALATE 15 g/100 mL
INACTIVE INGREDIENTS: ETHYLHEXYLGLYCERIN; CHAMOMILE FLOWER OIL; BIOSACCHARIDE GUM-1; PULLULAN; SQUALANE; ARNICA MONTANA; HYALURONATE SODIUM; STEARIC ACID; BETASIZOFIRAN; LYSOPHOSPHATIDYLCHOLINE, SOYBEAN; BUTYLOCTYL SALICYLATE; COCONUT ALKANES; HYDROLYZED JOJOBA ESTERS (ACID FORM); SODIUM STEAROYL GLUTAMATE; GLYCERYL STEARATE SE; GLYCERYL STEARATE CITRATE; ALOE VERA LEAF; XANTHAN GUM; HYDROGENATED CASTOR OIL; CITRUS AURANTIUM FLOWER; JASMINUM OFFICINALE WHOLE; ORYZA SATIVA WHOLE; PHENOXYETHANOL; WATER; COCO-CAPRYLATE/CAPRATE; GLYCERIN; POLYGLYCERYL-4 ISOSTEARATE

Vegan Collagen Every Day SPF 30

Active ingredients Purpose

Avobenzone 3% Sunscreen

Homosalate 15% Sunscreen

Octocrylene 10%5 Sunscreen

Octyl Salicylate 5% Sunscreen

Uses

Helps prevent sunburn. If used as directed with other sun protection measures (see Directions), decreases the risk of skin cancer & early skin aging caused by the sun.

INDICATIONS AND USAGE

If used as directed with other sun protection measures (see Directions), decreases the risk of skin cancer & early skin aging caused by the sun.

Warnings

For external use only. Do not use on damaged or broken skin. Stop use & ask a doctor if rash occurs. When using this product, keep out of eyes. Rinse with water to remove. Keep out of reach of children. If swallowed, get medical help or contact a Poison Control Center right away.

Keep out of reach of children.

Directions

Shake well before use. Apply liberally 15 minutes before sun exposure. Use a water resistant sunscreen if swimming or sweating.
Reapply after swimming or sweating. Reapply at least every 2 hours. Sun protection measures. Spending time in the sun increases your risk of skin cancer & early skin aging. To decrease this risk, regularly use a sunscreen with a broad spectrum SPF value of 15 or higher & other sun protection measures including: - limit time in the sun, especially from 10 a.m. - 2 p.m. - wear long-sleeve shirts, pants, hats & sunglasses. Children under 6 months: ask a doctor.

Inactive ingredients:

Aqua, Butyloctyl Salicylate, Coconut Alkanes, Coco-Caprylate/Caprate, Aloe Barbadensis Leaf Juice, Glycerin, Hydrolyzed Jojoba Esters, Glyceryl Stearate, Glyceryl Stearate Citrate, Sodium Stearoyl Glutamate, Polyglyceryl-4 Isostearate, Stearic Acid, Lysolecithin, Sclerotium Gum, Xanthan Gum, Pullulan, Hydrogenated Castor Oil, Sr-Hydrozoan Polypeptide-1 (Vegan Collagen), Sodium Hyaluronate, Citrus Aurantium Dulcis (Orange) Flower Extract, Jasminum Officinale (Jasmine) Extract, Chamomilla Recutita (Matricaria) Flower Extract, Arnica Montana Extract, Squalane, Oryza Sativa (Rice) Starch, Biosaccharide Gum-1, Phenoxyethanol, Ethylhexylglycerin, Parfum*.

*our scent blend with natural and/or essential oils

Other information

Protect this product from excessive heat & direct sun.

Questions or comments?

Call toll free 1-888-322-2466
Pacifica Beauty LLC Portland, Oregon